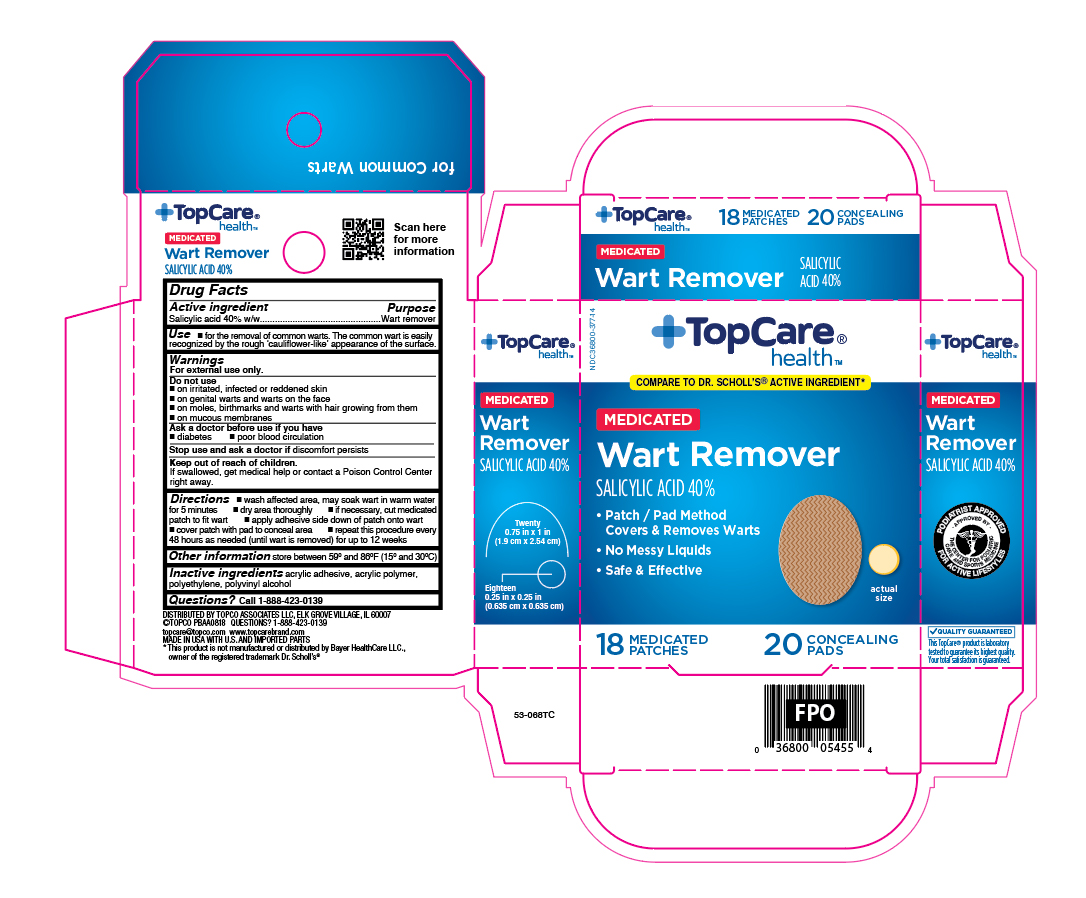 DRUG LABEL: Salicylic acid
NDC: 36800-377 | Form: PLASTER
Manufacturer: Topco Associates LLC
Category: otc | Type: HUMAN OTC DRUG LABEL
Date: 20260115

ACTIVE INGREDIENTS: SALICYLIC ACID 0.4 g/18 1
INACTIVE INGREDIENTS: HIGH DENSITY POLYETHYLENE

TopCare Wart Removers

Active ingredient

Salicylic acid 40%w/w

Purpose

Wart remover

Use

for the removal of common warts. The common wart is easily recognized by the rough 'cauliflower-like' appearance of the surface.

Warnings

For external use only.

Do not use

- on irritated, infected or reddened skin
- on genital warts and warts on the face
- on moles, birthmarks and warts with hair growing from them
- on mucous membranes

Ask a doctor before use if you have

- diabetes
- poor blood circulation

Stop use and ask a doctor if

discomforts persists

Keep out of reach of children.

If swallowed, get medical help or contact a Poison Control Center right away.

Directions

- wash affected area: may soak wart in warm water for 5 minutes
- dry area thoroughly
- if necessary, cut medicated patch to fit wart
- apply adhesive side down of patch onto wart
- cover patch with pad to conceal area
- repeat this procedure every 48 hours as needed (until wart is removed) for up to 12 weeks

Other information

store between 59°F to 86°F (15°C to 30°C)

Inactive ingredients

acrylic adhesive,acrylic polymer, polyethylene, polyvinyl alcohol

Questions?

call 1-888-423-0139

Principal Display Panel

TopCare

health

MEDICATED

Wart Remover

SALICYLIC ACID 40%

- Patch / Pad Method

Covers & Removes Warts

- No Messy Liquids
- Safe & Effective

18 MEDICATED PATCHES 20 CONCEALING PADS